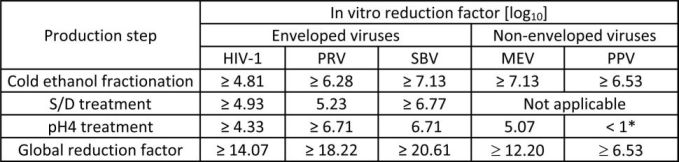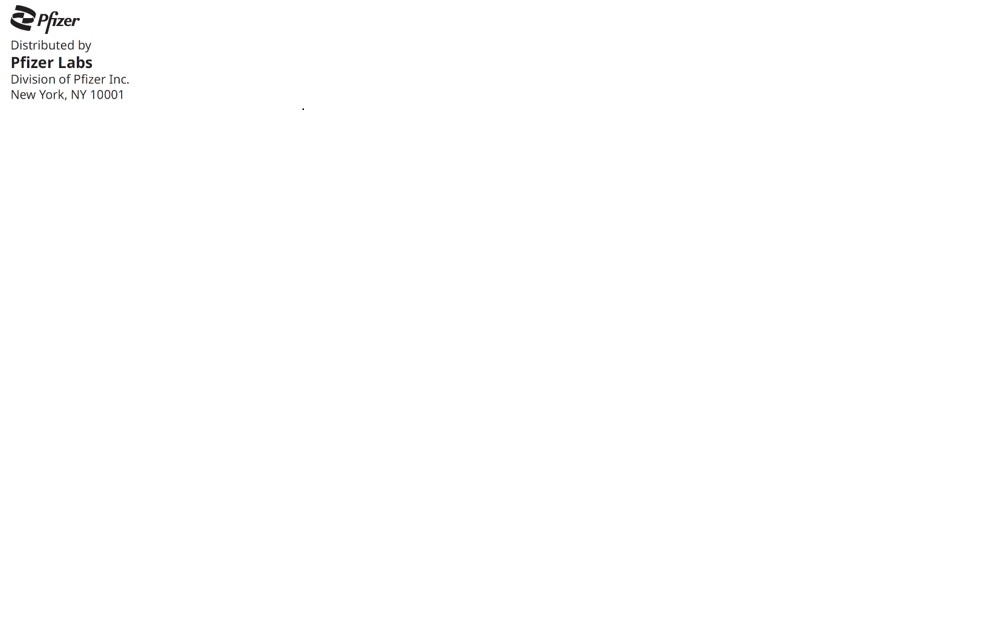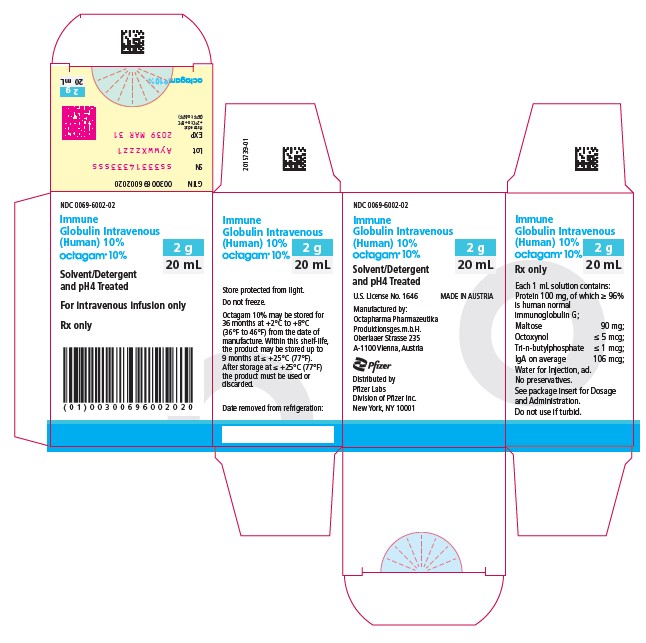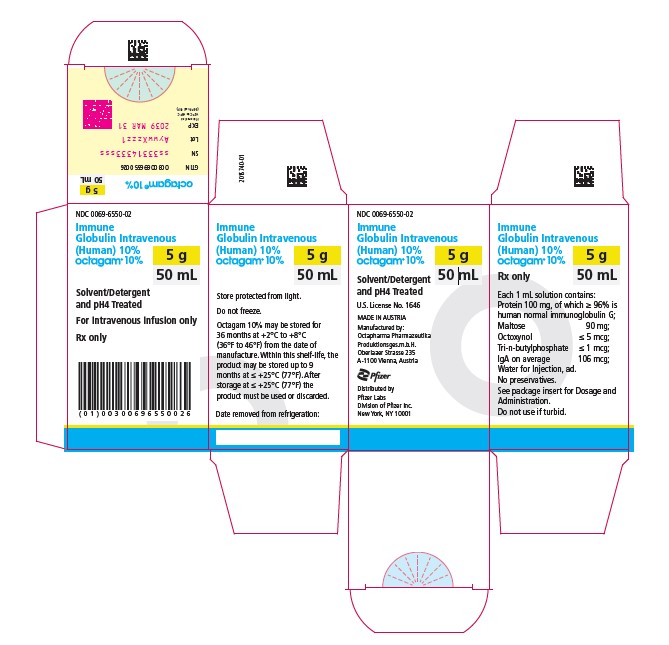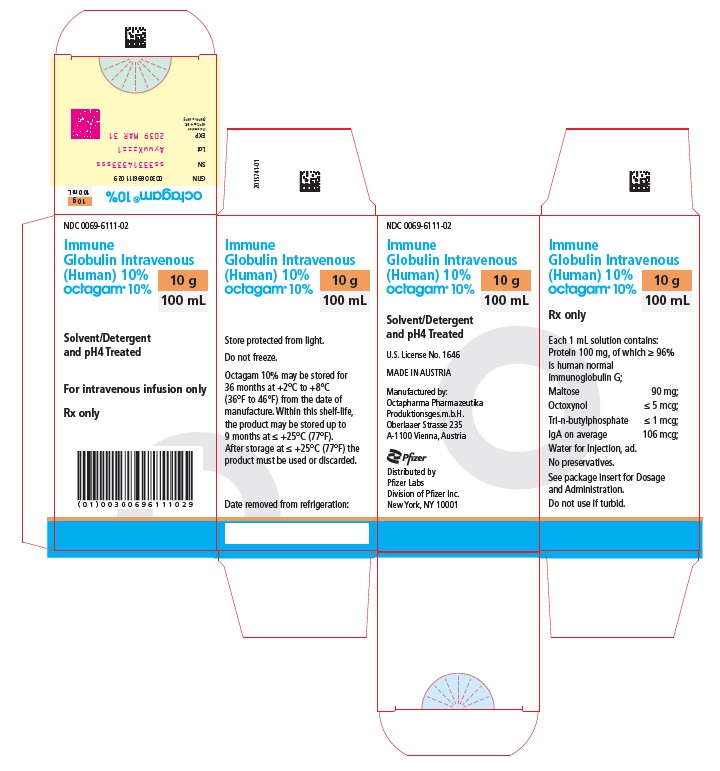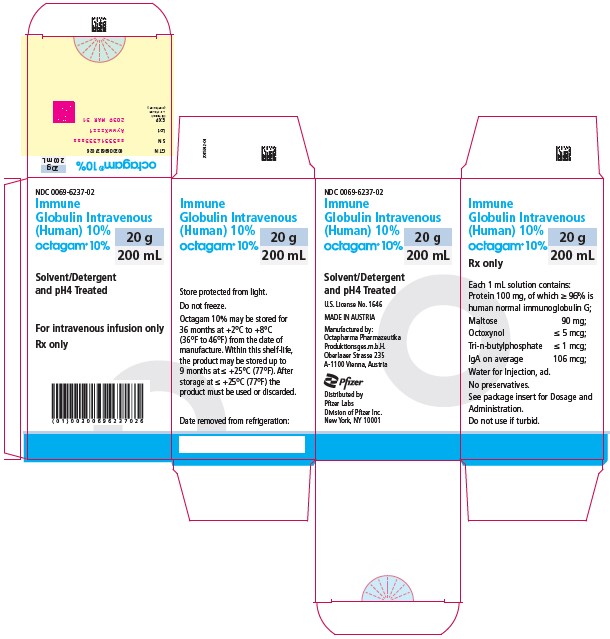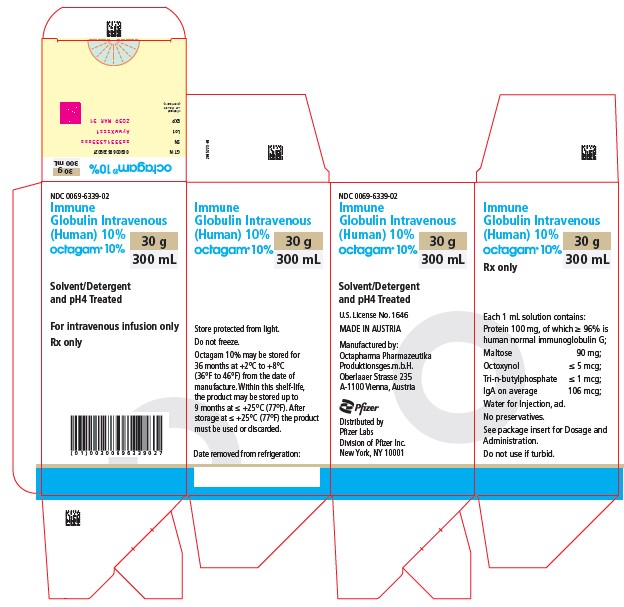 DRUG LABEL: Octagam Immune Globulin (Human)
NDC: 0069-6339 | Form: SOLUTION
Manufacturer: Pfizer Laboratories Div Pfizer Inc
Category: other | Type: PLASMA DERIVATIVE
Date: 20240126

ACTIVE INGREDIENTS: HUMAN IMMUNOGLOBULIN G 100 mg/1 mL

HIGHLIGHTS OF PRESCRIBING INFORMATION

These highlights do not include all the information needed to use Octagam 10% safely and effectively. See full prescribing information for Octagam 10%.
Octagam 10% [Immune Globulin Intravenous (Human)]
liquid solution for intravenous administration
Initial U.S. Approval: 2014

RECENT MAJOR CHANGES

Indications and Usage (1.2) 06/2021

Dosage and Administration (2.1) 06/2021

WARNING

WARNING: THROMBOSIS, RENAL DYSFUNCTION AND ACUTE RENAL FAILURE

See full prescribing information for complete boxed warning

Thrombosis may occur with immune globulin intravenous (IGIV) products, including Octagam 10%. Risk factors may include: advanced age, prolonged immobilization, hypercoagulable conditions, history of venous or arterial thrombosis, use of estrogens, indwelling vascular catheters, hyperviscosity, and cardiovascular risk factors.

Renal dysfunction, acute renal failure, osmotic nephropathy, and death may occur with the administration of Immune Globulin Intravenous (Human) (IGIV) products in predisposed patients. Renal dysfunction and acute renal failure occur more commonly in patients receiving IGIV products containing sucrose. Octagam 10% does not contain sucrose.

For patients at risk of thrombosis, renal dysfunction or renal failure, administer Octagam 10% at the minimum infusion rate practicable. Ensure adequate hydration in patients before administration. Monitor for signs and symptoms of thrombosis and assess blood viscosity in patients at risk for hyperviscosity

1 INDICATIONS AND USAGE

Octagam 10% is an immune globulin intravenous (human) liquid preparation indicated for the treatment of:

Chronic immune thrombocytopenic purpura (ITP) in adults (1.1)

Dermatomyositis (DM) in adults (1.2).

2 DOSAGE AND ADMINISTRATION

For intravenous use only.

Indication | Dose | Initial Infusion rate | Maintenance Infusion Rate (if tolerated)
Chronic ITP | 2 g/kg divided in equal doses given over 2 consecutive days | 1.0 mg/kg/min(0.01 mL/kg/min) | Up to 12.0 mg/kg/min(Up to 0.12 mL/kg/min)
Dermato-myositis | 2 g/kg divided in equal doses given over 2-5 consecutive days every 4 weeks | 1.0 mg/kg/min(0.01 mL/kg/min) | Up to 4.0 mg/kg/min(Up to 0.04 mL/kg/min)

Patients with dermatomyositis are at increased risk for thromboembolic Events; monitor carefully and do not exceed an infusion rate of 0.04 ml/kg/min.

Ensure that patients with pre-existing renal insufficiency are not volume depleted; discontinue Octagam 10% if renal function deteriorates (2 , 5.2).

For patients at risk of renal dysfunction or thrombotic events, administer Octagam 10% at the minimum infusion rate practicable (5.2 , 5.5).

3 DOSAGE FORMS AND STRENGTHS

Solution containing 10% IgG (100 mg/mL) (3 , 16)

4 CONTRAINDICATIONS

History of anaphylactic or severe systemic reactions to human immunoglobulin (4)

IgA deficient patients with antibodies against IgA and a history of hypersensitivity (4)

5 WARNINGS AND PRECAUTIONS

IgA-deficient patients with antibodies against IgA are at greater risk of developing severe hypersensitivity and anaphylactic reactions to Octagam 10%. Epinephrine should be available immediately to treat any severe acute hypersensitivity reactions (5.1).

Monitor renal function, including blood urea nitrogen and serum creatinine, and urine output in patients at risk of developing acute renal failure (5.2).

Falsely elevated blood glucose readings may occur during and after the infusion of Octagam 10% with testing by some glucometers and test strip systems (5.3).

Hyperproteinemia, increased serum osmolarity and hyponatremia may occur in patients receiving Octagam 10% (5.4).

Hemolysis that is either intravascular or due to enhanced red blood cell sequestration can develop subsequent to Octagam 10% treatments. Risk factors for hemolysis include high doses and non-O-blood group. Closely monitor patients for hemolysis and hemolytic anemia (5.6).

Aseptic Meningitis Syndrome may occur in patients receiving Octagam 10%, especially with high doses or rapid infusion (5.7).

Monitor patients for pulmonary adverse reactions (transfusion-related acute lung injury (TRALI)) (5.8).

Octagam 10% is made from human plasma and may contain infectious agents, e.g. viruses and, theoretically, the Creutzfeldt-Jakob disease agent (5.9).

6 ADVERSE REACTIONS

Chronic ITP: The most common adverse reactions reported in greater than 5% of subjects during a clinical trial were headache, fever and increased heart rate (6).

Dermatomyositis: The most common adverse reactions reported in greater than 5% of subjects during a clinical trial were headache, fever, nausea, vomiting, increased blood pressure, chills, musculoskeletal pain, increased heart rate, dyspnea, and infusions site reactions (6)

To report SUSPECTED ADVERSE REACTIONS, contact Pfizer Inc. at 1-800-438-1985 or FDA at 1-800-FDA-1088 or www.fda.gov/medwatch.

7 DRUG INTERACTIONS

The passive transfer of antibodies may:

Confound the results of serological testing (7).

Interfere with the immune response to live viral vaccines, such as measles, mumps, and rubella (7).

8 USE IN SPECIFIC POPULATIONS

Pregnancy: no human or animal data. Use only if clearly needed (8.1).

Geriatric Use: In patients over age 65 or in any person at risk of developing renal insufficiency, do not exceed the recommended dose, and infuse Octagam 10% at the minimum infusion rate practicable (8.5).

_______________________________________________________________________________________________________________________________________

FULL PRESCRIBING INFORMATION

Octagam 10% [Immune Globulin Intravenous (Human)] Liquid Preparation

WARNING

THROMBOSIS, RENAL DYSFUNCTION AND ACUTE RENAL FAILURE

- Thrombosis may occur with immune globulin intravenous (IGIV) products, including Octagam 10%. Risk factors may include: advanced age, prolonged immobilization, hypercoagulable conditions, history of venous or arterial thrombosis, use of estrogens, indwelling central vascular catheters, hyperviscosity, and cardiovascular risk factors. Thrombosis may occur in the absence of known risk factors. (See WARNING and PRECAUTIONS [ 5.5 ], PATIENT COUNSELING INFORMATION [ 17 ]

- Renal dysfunction, acute renal failure, osmotic nephrosis, and death may occur in predisposed patients who receive IGIV products, including Octagam 10%. Patients predisposed to renal dysfunction include those with a degree of pre-existing renal insufficiency, diabetes mellitus, age greater than 65, volume depletion, sepsis, paraproteinemia, or patients receiving known nephrotoxic drugs. Renal dysfunction and acute renal failure occur more commonly in patients receiving IGIV product containing sucrose. Octagam 10% does not contain sucrose.

- For patients at risk of thrombosis, renal dysfunction or acute renal failure, administer Octagam 10% at the minimum dose and infusion rate practicable. Ensure adequate hydration in patients before administration. Monitor for signs and symptoms of thrombosis and assess blood viscosity in patients at risk for hyperviscosity. (See DOSAGE and ADMINISTRATION [ 2.3 ], WARNINGS and PRECAUTIONS [ 5.5 ])

1 INDICATIONS AND USAGE

1.1 Chronic Immune Thrombocytopenic Purpura (ITP)

Octagam 10% is indicated for the treatment of chronic immune thrombocytopenic purpura to rapidly raise platelet counts to control or prevent bleeding in adults.

1.2 Dermatomyositis (DM)

Octagam 10% is indicated for the treatment of dermatomyositis in adults.

2 DOSAGE AND ADMINISTRATION

For intravenous use only.

2.1 Dosage

Indication | Dose | Initial Infusion rate | Maintenance Infusion Rate (if tolerated)
Chronic ITP | 2 g/kg divided in equal doses given on 2 consecutive days | 1.0 mg/kg/min(0.01 mL/kg/min) | Up to 12.0 mg/kg/min(Up to 0.12 mL/kg/min)
Dermatomyositis (DM) | 2 g/kg divided in equal doses given over 2-5 consecutive days every 4 weeks | 1.0 mg/kg/min(0.01 mL/kg/min) | Up to 4.0 mg/kg/min(Up to 0.04 mL/kg/min)

2.2 Preparation and Handling

- Parenteral products should be inspected visually for particulate matter and discoloration prior to administration, whenever solution and container permit. Do not use if Octagam 10% is turbid and/or if discoloration is observed.
- Do not mix Octagam 10% with other medicinal products or administer simultaneously with other intravenous preparation in the same infusion set. Do not mix Octagam 10% with immune globulin intravenous (IGIV) products from other manufacturers.
- Do not freeze Octagam 10%. Do not use solutions that have been frozen.
- Octagam 10% contains no preservative. Octagam 10% bottle is for single use only. Use promptly any bottle that has been entered or opened, and discard partially used bottles.
- The content of Octagam 10% bottles may be pooled under aseptic conditions into sterile infusion bags and infused within 8 hours after pooling.
- Do not use after expiration date.
- Do not dilute Octagam 10%.
- The infusion line may be flushed before and after administration of Octagam 10% with either normal saline or 5% dextrose in water.

2.3 Administration

- Administer Octagam 10%, which is to be at room temperature, only by the intravenous route.
- Octagam 10% is not supplied with an infusion set. If an in-line filter is used the pore size should be 0.2 – 200 microns.
- Do not use a needle of larger than 16 gauge to prevent the possibility of coring. Insert needle only once, within the stopper area delineated (by the raised ring for penetration). Penetrate the stopper perpendicular to its plane and within the ring.

For rate of administration, see Table 1.

Table 1

Rate of Administration | mg/kg/min (mg/kg/hour) | mL/kg/min
first 30 min | 1 (60) | 0.01
next 30 min, if above is tolerated | 2 (120) | 0.02
next 30 min, if above is tolerated | 4 (240) | 0.04*
next 30 min, if above is tolerated | 8 (480) | 0.08
Maximum | ≤ 12 (≤720) | ≤0.12

*Patients with dermatomyositis are at increased risk for thromboembolic events; monitor carefully and do not exceed an infusion rate of 0.04 ml/kg/min.

- Monitor the patient carefully throughout the infusion. Certain adverse drug reactions may be related to the rate of infusion. Slowing or stopping the infusion usually allows the symptoms to disappear promptly. Once the symptoms subside, the infusion may then be resumed at a lower rate.

- Ensure that patients with pre-existing renal insufficiency are not volume depleted. For patients at risk of renal dysfunction or thromboembolic events, administer Octagam 10% at the minimum infusion rate practicable, not to exceed 3.3 mg/kg/min (0.03 mL/kg/min). Discontinue Octagam 10% if renal function deteriorates.

3 DOSAGE FORMS AND STRENGTHS

Solution containing 10% IgG (100 mg/mL) (See How Supplied/Storage and Handling (16)).

4 CONTRAINDICATIONS

- Octagam 10% is contraindicated in patients who have a history of severe systemic hypersensitivity reactions, such as anaphylaxis, to human immunoglobulin.
- Octagam 10% contains trace amounts of IgA (average 106 µg/mL in a 10% solution). It is contraindicated in IgA-deficient patients with antibodies against IgA and history of hypersensitivity .

5 WARNINGS AND PRECAUTIONS

5.1 Hypersensitivity

Severe hypersensitivity reactions may occur (See Contraindications (4)) .[ 1 ] In case of hypersensitivity, discontinue Octagam 10% infusion immediately and institute appropriate treatment. Epinephrine should be immediately available for treatment of severe acute hypersensitivity reactions.

Octagam 10% contains trace amounts of IgA (average 106 µg/mL in a 10% solution). IgA-deficient patients with antibodies against IgA are at greater risk of developing severe hypersensitivity and anaphylactoid reactions when administered Octagam 10% (See Contraindications (4)) .

Octagam 10% may cause hypersensitivity reactions in patients with corn allergy. Octagam 10% contains maltose, a disaccharide sugar which is derived from corn.

5.2 Renal Dysfunction/Failure

Renal dysfunction, acute renal failure, osmotic nephropathy, and death may occur upon use of Octagam 10% in predisposed patients.

Ensure that patients are not volume depleted prior to the initiation of the infusion of Octagam 10%.

For patients at risk of renal dysfunction because of pre-existing renal insufficiency or predisposition to acute renal failure (such as individuals with diabetes mellitus, age greater than 65, volume depletion, sepsis, paraproteinemia, or those receiving known nephrotoxic drugs), administer Octagam 10% at the minimum infusion rate practicable, not to exceed 3.3mg/kg/min (0.03mL/kg/min) (See Boxed Warning, and Dosage and Administration (2)).

Periodic monitoring of renal function tests and urine output is particularly important in patients judged to be at risk of developing acute renal failure. Assess renal function, including a measurement of blood urea nitrogen (BUN)/serum creatinine, prior to the initial infusion of Octagam 10% and again at appropriate intervals thereafter. If renal function deteriorates, consider discontinuation of the product.

5.3 Blood Glucose Monitoring

Some glucose monitoring systems give falsely elevated glucose readings because they interpret the maltose in Octagam 10% as glucose.[ 2 ] This occurs in systems that use glucose dehydrogenase pyrroloquinoline quinone (GDH-PQQ) or glucose-dye-oxidoreductase methods for detecting blood glucose. Inaccurate glucose readings can cause inappropriate administration of insulin and resultant potentially life-threatening hypoglycemia. Also, true hypoglycemia may go undetected when masked by a falsely elevated glucose reading.

Monitor glucose levels in diabetic patients with a glucose-specific method only. Review the product information of blood glucose testing systems, including the test strips, to determine if the system is appropriate to use with maltose-containing parenteral products. Contact the manufacturer if there is any uncertainty about the system.

5.4 Hyperproteinemia, Increased Serum Viscosity and Hyponatremia

Hyperproteinemia, increased serum viscosity and hyponatremia may occur in patients receiving Octagam 10% therapy. It is clinically critical to distinguish true hyponatremia from pseudohyponatremia related to hyperproteinemia with concomitant decreased calculated serum osmolality or elevated osmolar gap, because treatment aimed at decreasing serum free water in patients with pseudohyponatremia may lead to volume depletion, a further increase in serum viscosity and a higher risk of thromboembolic events.[ 3 ]

5.5 Thrombosis

Thrombosis may occur following treatment with immune globulin products, including Octagam 10%. Risk factors may include: advanced age, prolonged immobilization, hypercoagulable conditions, history of venous or arterial thrombosis, use of estrogens, indwelling central vascular catheters, hyperviscosity, and cardiovascular risk factors. Thrombosis may occur in the absence of known risk factors.

Consider baseline assessment of blood viscosity in patients at risk for hyperviscosity, including those with cryoglobulins, fasting chylomicronemia / markedly high triacylglycerols (triglycerides), or monoclonal gammopathies. For patients at risk of thrombotic events, administer Octagam 10% at the minimum dose and infusion rate practicable. Ensure adequate hydration in patients before administration. Monitor for signs and symptoms of thrombosis and assess blood viscosity in patients at risk for hyperviscosity. [ 4-6 ] (See BOXED WARNING, DOSAGE and ADMINSTRATION [ 2.3 ], PATIENT COUNSELING INFORMATION [ 17 ])

5.6 Hemolysis

Octagam 10% may contain blood group antibodies that can act as hemolysins and induce in vivo coating of red blood cells (RBCs) with immunoglobulin, causing a positive direct antiglobulin test (DAT) (Coombs’ test) result and hemolysis. Delayed hemolytic anemia can develop subsequent to IGIV therapy due to enhanced RBC sequestration and acute hemolysis, consistent with intravascular hemolysis, has been reported. Cases of severe hemolysis-related renal dysfunction/failure or disseminated intravascular coagulation have occurred following infusion of IGIV.

The following risk factors may be associated with the development of hemolysis following IGIV administration: high doses (e.g. ≥ 2 g/kg), given either as a single administration or divided over several days, and non-O blood group.[ 7 ]. Other individual patient factors, such as an underlying inflammatory state (as may be reflected by, for example, elevated C-reactive protein or erythrocyte sedimentation rate), have been hypothesized to increase the risk of hemolysis following administration of IGIV.[ 8 ], but their role is uncertain. Hemolysis has been reported following administration of IGIV for a variety of indications, including ITP.

Closely monitor patients for clinical signs and symptoms of hemolysis, particularly patients with risk factors noted above. Consider appropriate laboratory testing in higher risk patients, including measurement of hemoglobin or hematocrit prior to infusion and within approximately 36 to 96 hours post infusion. If clinical signs and symptoms of hemolysis or a significant drop in hemoglobin or hematocrit have been observed, perform confirmatory laboratory testing. If transfusion is indicated for patients who develop hemolysis with clinically compromising anemia after receiving IGIV, perform adequate cross-matching to avoid exacerbating on-going hemolysis.

5.7 Aseptic Meningitis Syndrome

Aseptic meningitis syndrome (AMS) may occur with Octagam treatment. Discontinuation of treatment has resulted in remission of AMS within several days without sequelae. The syndrome usually begins within several hours to two days following rapid infusion with Octagam treatment. It is characterized by symptoms and signs including severe headache, nuchal rigidity, drowsiness, fever, photophobia, painful eye movements, nausea and vomiting. Cerebrospinal fluid (CSF) studies frequently reveal pleocytosis up to several thousand cells per cubic millimeter, predominantly from the granulocytic series, and elevated protein levels up to several hundred mg/dl, but negative culture results. Conduct a thorough neurological examination in patients exhibiting such symptoms and signs, including CSF studies, to rule out other causes of meningitis. It appears that patients with a history of migraine may be more susceptible.[ 9 ]

AMS may occur more frequently following high doses (≥2 g/kg) and/or rapid infusion of IGIV.

5.8 Transfusion-Related Acute Lung Injury (TRALI)

Noncardiogenic pulmonary edema [Transfusion-Related Acute Lung Injury (TRALI)] may occur in patients administered IGIV.[ 10 ] TRALI is characterized by severe respiratory distress, pulmonary edema, hypoxemia, normal left ventricular function, and fever. Signs and symptoms typically appear within 1 to 6 hours after transfusion. Patients with TRALI may be managed using oxygen therapy with adequate ventilatory support.

Monitor recipients of Octagam 10% for pulmonary adverse reactions. If TRALI is suspected, perform appropriate tests for the presence of anti-HLA and anti-neutrophil antibodies in the product.

5.9 Transmission of Infectious Agents

Because Octagam 10% is made from human blood, it may carry a risk of transmitting infectious agents, e.g., viruses and theoretically, the Creutzfeldt-Jakob disease (CJD) agent. Report all infections thought by a physician or other healthcare provider to have been possibly transmitted by this product to Pfizer Inc. at 1-800-438-1985. Discuss the risks and benefits of Octagam 10% with the patient before prescribing or administering this product.

5.10 Monitoring Laboratory Tests

- After infusion of immunoglobulin, the transitory rise of the various passively transferred antibodies in the patient’s blood may yield positive serological testing results, with the potential for misleading interpretation.
- Passive transmission of antibodies to erythrocyte antigens (e.g. A, B, and D) may cause a positive direct or indirect antiglobulin (Coombs’) test. Clinically assess patients with known renal dysfunction, diabetes mellitus, age greater than 65, volume depletion, sepsis, paraproteinemia, or those receiving nephrotic agents, and monitor as appropriate (BUN; serum creatinine, urine output) during therapy with Octagam 10%.
- Consider baseline assessment of blood viscosity in patients at risk for hyperviscosity, including those with polycythemia, cryoglobulins, fasting chylomicronemia/markedly high triglycerides, or monoclonal gammopathies.
- Consider measuring hemoglobin or hematocrit at baseline and approximately 36 to 96 hours post infusion in patients at higher risk of hemolysis. If signs and/or symptoms of hemolysis are present after an infusion of Octagam 10%, perform appropriate laboratory testing for confirmation.
- If TRALI is suspected, perform appropriate tests for the presence of anti-neutrophil antibodies in both the product and patient’s serum.

6 ADVERSE REACTIONS

Chronic Immune Thrombocytopenic Purpura (ITP)

The most common adverse reactions observed in > 5% of clinical study subjects with ITP were headache, fever, and increased heart rate.

Dermatomyositis (DM)

The most common adverse reactions observed in > 5% of clinical study subjects with DM were headache, fever, nausea, vomiting, increased blood pressure, chills, musculoskeletal pain, increased heart rate, dyspnea, and infusions site reactions.

6.1 Clinical Trials Experience

Because clinical trials are conducted under widely varying conditions, adverse reaction rates observed in the clinical trials of a product cannot be directly compared to rates in the clinical trials of another product and may not reflect the rates observed in clinical practice.

Treatment of Chronic Immune Thrombocytopenic Purpura (ITP) in Adults

In a prospective, open-label, single-arm, multicenter study 116 subjects with newly diagnosed or chronic ITP received Octagam 10% at a dose of 2 g/kg, administered daily as 1 g/kg intravenous infusions on 2 consecutive days. In the initial study phase, the infusion rate allowed for Octagam 10% administration was up to 6 mg/kg/min [0.06 mL/kg/min], which was achieved in 24 of 26 subjects (92%). Subsequently, the maximum infusion rate allowed was 12 mg/kg/min [0.12mL/kg/min], and 54 (60%) of 90 subjects received Octagam 10% at this rate in the second phase of the trial.

Pre-medication to alleviate potential adverse drug reactions was allowed, and was only administered to 1 (0.9%) of the 116 patients.

The investigators judged 129 (54%) of the temporally associated ("infusional") adverse reactions (AR) in 62 patients to be at least possibly related to the infusion of Octagam 10%. The most common causally related ARs observed in > 5% of subjects are shown in Table 2.

Table 2: Drug-related Adverse Reactions Experienced by >5% of Subjects

Reactions | No. of Subjects (% of Subjects [n=116])
Headache | 29 (25)
Pyrexia | 17 (15)
Heart Rate Increased | 13 (11)

Table 3: ARs in >5% Subjects During and Within 72 Hours After the End of 2-Days Treatment Cycle, Irrespective of Causality

Reactions | No. of Subjects (% of Subjects [n=116])
Headache | 35 (30)
Heart Rate Increased | 25 (22)
Pyrexia | 20 (17)
Heart Rate Decreased | 18 (16)
Hypertension | 7 (6)

One subject experienced a serious adverse reaction (headache).

Treatment of Dermatomyositis (DM) in Adults

In a prospective, double-blind, randomized, placebo-controlled, multicenter study with two study periods, 95 adults with DM were enrolled. In the First Period (16 weeks), 47 subjects received 2 g/kg Octagam 10% and 48 subjects received placebo every 4 weeks for 4 infusion cycles. In the following 6-month open-label Extension Period, 91 subjects received 6 infusion cycles of Octagam 10% (one infusion cycle every 4 weeks). One infusion cycle comprised of all infusions administered over 2-5 days.

Table 4 and Table 5 summarize the most frequent adverse reactions (ARs) that occurred in >5% of subjects with DM in the clinical study. Premedication for infusions was given to 21.3% of patients in the Octagam group.

During the study, no subject met the criteria for a hemolytic transfusion reaction (HTR). No deaths were reported during the study.

The following serious adverse reactions were observed in the study: muscle spasms and dyspnea in one subject, loss of consciousness in one subject, and thromboembolic events (TEEs) in five subjects, including deep vein thrombosis and pulmonary embolism in one subject, cerebrovascular accident in one subject, cerebral infarction in one subject, hypoesthesia in one subject and pulmonary embolism in one subject. For risk factors for TEE see also [ 5.5 ]).

Table 4: Drug-related Adverse Reactions Experienced by >5% of Subjects

Reactions | No. of Subjects (% of Subjects [n=95])
Headache | 40 (42)
Pyrexia | 18 (19)
Nausea | 15 (16)
Vomiting | 8 (8)
Chills | 7 (7)
Musculoskeletal pain | 7 (7)
Blood pressure increased | 6 (6)

Table 5: ARs in >5% of Subjects During and Within 72 Hours After End of Infusion Cycle, Irrespective of Causality

Reactions | No. of Subjects (% of Subjects [n=95])
Headache | 44 (46)
Pyrexia | 19 (20)
Nausea | 16 (17)
Vomiting | 8 (8)
Blood pressure increased | 8 (8)
Chills | 7 (7)
Musculoskeletal pain | 5 (5)
Heart Rate Increased | 5 (5)
Dyspnea | 5 (5)
Infusion site reactions | 5 (5)

6.2 Postmarketing Experience

Because postmarketing reporting of adverse reactions is voluntary and from a population of uncertain size, it is not always possible to reliably estimate the frequency of these reactions or establish a causal relationship to product exposure.

The following adverse reactions have been identified during post-approval use of Octagam.

Blood and lymphatic system disorders
Leucopenia, hemolytic anemia

Immune system disorders
Hypersensitivity, anaphylactic shock, anaphylactic reaction, anaphylactoid reaction, angioedema, face edema

Metabolic and nutritional disorders
Fluid overload, (pseudo)hyponatremia

Psychiatric disorders
Agitation, confusional state, anxiety, nervousness

Nervous system disorders
Cerebrovascular accident, loss of consciousness, speech disorder, aseptic meningitis, migraine, dizziness, paresthesia, hypoesthesia, tremor, photophobia,

Eye disorders
Visual impairment

Cardiac disorders
Myocardial infarction, angina pectoris, bradycardia, tachycardia, palpitations, cyanosis

Vascular disorders
Hypotension, thrombosis, circulatory collapse, peripheral circulatory failure, hypertension, phlebitis, pallor

Respiratory, thoracic and mediastinal disorders
Respiratory failure, pulmonary embolism, pulmonary edema, bronchospasm, dyspnea, cough, hypoxia

Gastrointestinal disorders
Nausea, vomiting, diarrhea, abdominal pain

Skin and subcutaneous tissue disorders
Eczema, skin exfoliation, urticaria, rash, rash erythematous, dermatitis, erythema, pruritus, alopecia

Musculoskeletal and connective tissue disorders
Back pain, arthralgia, myalgia, pain in extremity, neck pain, muscle spasms, muscular weakness, musculoskeletal stiffness

Renal and urinary disorders
Acute renal failure, renal pain

General disorders and administration site conditions
Fatigue, oedema, injection site reaction, pyrexia, influenza-like illness, chills, chest pain, chest discomfort, hot flush, flushing, feeling hot, feeling cold, hyperhidrosis, malaise, lethargy, asthenia, burning sensation

Investigations
Hepatic enzymes increased, falsely elevated blood glucose level

Injury, poisoning and procedural complications
Transfusion-related acute lung injury

7 DRUG INTERACTIONS

Admixtures of Octagam 10% with other drugs and intravenous solutions have not been evaluated. It is recommended that Octagam 10% be administered separately from other drugs or medications which the patient may be receiving. Do not mix the product.

Do not mix Octagam 10% with IGIVs from other manufacturers.

Passively transferred antibodies in immunoglobulin preparations can confound the results of serological testing.

Antibodies in Octagam 10% may interfere with the response to live viral vaccines, such as measles, mumps, and rubella. Inform physicians of recent therapy with Octagam 10%, so that administration of live viral vaccines, if indicated, can be appropriately delayed for 3 or more months from the time of Octagam 10% administration.

8 USE IN SPECIFIC POPULATIONS

8.1 Pregnancy

Risk Summary

No human data are available to indicate the presence or absence of drug-associated risk. Animal reproduction studies have not been conducted with Octagam 10%. It is not known whether Octagam 10% can cause foetal harm when administered to a pregnant woman or can affect reproduction capacity. Immune globulins cross the placenta from maternal circulation increasingly after 30 weeks of gestation. Octagam 10% should be given to pregnant women only if clearly needed. In the U.S. general population, the estimated background risk of major birth defects and miscarriage in clinically recognized pregnancies is 2-4% and 15-20%, respectively.

8.2 Lactation

Risk Summary

No human data are available to assess the presence or absence of Octagam 10% in human milk, the effects of Octagam 10% on the breastfed child, and the effects of Octagam 10% on milk production/excretion. The developmental and health benefits of breastfeeding should be considered along with the mother’s clinical need for Octagam 10% liquid and any potential adverse effects on the breastfed infant from Octagam 10% liquid or from the underlying maternal condition. Immunoglobulins are excreted into the milk and may contribute to the transfer of protective antibodies to the neonate.

8.4 Pediatric Use

The safety and effectiveness of Octagam 10% has not been established in pediatric patients with ITP or DM.

8.5 Geriatric Use

Patients > 65 years of age may be at increased risk for developing certain adverse reactions such as thromboembolic events and acute renal failure (See Boxed Warnings and Thrombotic Events (5.5) and Renal Failure (5.2) . Do not exceed recommended doses in this population, and the applied infusion rate should be the minimum practicable. Clinical studies of Octagam 10% did not include sufficient numbers of subjects > 65 years to determine whether they respond differently from younger subjects. During the First Period (placebo-controlled) of the DM trial, 11 patients over 65 years were treated with Octagam.

10 OVERDOSAGE

With intravenous administration, overdose of Octagam 10% may lead to fluid overload and hyperviscosity. Patients at risk of complications of fluid overload and hyperviscosity include elderly patients and those with cardiac or renal impairment.

11 DESCRIPTION

Immune Globulin Intravenous (Human), Octagam 10%, is a solvent/detergent (S/D)-treated, sterile preparation of highly purified immunoglobulin G (IgG) derived from large pools of human plasma. Octagam 10% is a solution for infusion to be administered intravenously.

This preparation contains approximately 100 mg of protein per mL (10%) of which not less than 96% is normal human immunoglobulin G. Octagam 10% contains not more than 3% aggregates, not less than 94% monomers and dimers and not more than 3% fragments. On average, the product contains 106 µg/mL of IgA and even lower amounts of IgM.

The sodium content of the final solution is not more than 30 mmol/L and the pH is between 4.5 and 5.0. The osmolality is 310 - 380 mosmol/kg.

The manufacturing process for Octagam 10% isolates IgG without additional chemical or enzymatic modification, and the Fc portion is maintained intact Octagam 10% contains the IgG antibody activities present in the donor population. IgG subclasses are fully represented with the following approximate percents of total IgG: IgG 1 is 65%, IgG 2 is 30%, IgG 3 is 3% and IgG 4 is 2%.

Octagam 10% contains a broad spectrum of IgG antibodies against bacterial and viral agents that are capable of opsonization and neutralization of microbes and toxins. It contains maltose (90 mg/mL), but no preservatives or sucrose.

All units of human plasma used in the manufacture of Octagam 10% are provided by FDA-approved blood establishments, and are tested by FDA-licensed serological tests for HBsAg, antibodies to HCV and HIV and Nucleic Acid Test (NAT) for HCV and HIV-1 and found to be non-reactive (negative).

The product is manufactured by the cold ethanol fractionation process followed by ultrafiltration and chromatography. The manufacturing process includes treatment with an organic S/D mixture composed of tri-n-butyl phosphate (TNBP) and Triton X-100 (Octoxynol). The Octagam 10% manufacturing process shows significant viral reduction in in vitro studies (Table 6). These reductions are achieved through a combination of process steps including cold ethanol fractionation, S/D treatment and pH 4 treatment.

Table 6: In vitro reduction factor during Octagam 10% manufacturing

*not calculated for global LRF

HIV-1: Human Immunodeficiency Virus - 1

PRV: Pseudorabies Virus

SBV: Sindbis Virus

MEV: Mouse Encephalomyelitis Virus

PPV: Porcine Parvovirus

12 CLINICAL PHARMACOLOGY

12.1 Mechanism of Action

The mechanism of action of immunoglobulins in the treatment of chronic ITP or in Dermatomyositis has not been fully elucidated.

12.3 Pharmacokinetics

Pharmacokinetic studies with Octagam 10% have not been performed in patients with chronic ITP nor in patients with Dermatomyositis.

13 NONCLINICAL TOXICOLOGY

13.1 Carcinogenesis, Mutagenesis, Impairment of Fertility

No studies were conducted on carcinogenesis, mutagenesis, or impairment of fertility with Octagam 10%.

Repeated-dose toxicity studies and genotoxic studies gave no evidence of carcinogenic properties of TNBP and Octoxynol.[ 11,12 ].

The results of in vitro and in vivo genotoxicity studies for TNBP and Octoxynol were negative. The results of studies on the embryotoxic and teratogenic properties of TNBP and Octoxynol in rats and rabbits at a wide range of i.v. doses were also negative.

13.2 Animal Toxicology and/or Pharmacology

No studies were conducted on pharmacology and pharmacokinetics with Octagam 10% in animals.

A variety of single-dose toxicity studies were performed for TNBP and Octoxynol alone or in combination: the lowest toxic dose of TNBP + Octoxynol (in a ratio of 1:5) was 10,000 mcg/kg BW in rats after intravenous administration. Studies on 13-week toxicity were performed for intravenous combinations of TNBP + Octoxynol in a broad dose range in dogs and rats: the lowest toxic dose for rats was local 60 mcg TNBP/kg + 300 mcg Octoxynol/kg BW (concentration: 0.0006% and 0.003%, respectively) and systemic 300 mcg TNBP/kg + 1,500 mcg Octoxynol/kg BW (concentration: 0.003% and 0.015%, respectively); the lowest toxic dose for dogs was local 50 mcg TNBP/kg + 250 mcg Octoxynol/kg BW (concentration: 0.005% and 0.025%, respectively) and systemic 500 mcg TNBP/kg + 2,500 mcg Octoxynol/kg BW (concentration: 0.05% and 0.25%, respectively).

A pharmacokinetic study was carried out in rats given 300 mcg of TNBP/kg and 1,500 mcg Octoxynol/kg BW i.v. The plasma half-life for TNBP was approximately 20 minutes. Octoxynol was not detected.

14 CLINICAL STUDIES

14.1 Treatment of Chronic Immune Thrombocytopenic Purpura

A prospective, open-label, single-arm, multicenter study assessed the efficacy, safety, and tolerability of Octagam 10% in 116 subjects with tentative newly diagnosed or chronic ITP and a platelet count of 20 x 10 ^9 /L or less. Subjects ranged in age from 17 to 88; 64% were female and 36% were male.

Subjects received a 2 g/kg dose of Octagam 10% administered as two daily 1 g/kg intravenous doses, given on 2 consecutive days. Pre-medication to alleviate potential adverse drug reactions was allowed but only given to 1 (0.9%) of 116 patients. In the initial study phase, the infusion rate allowed for Octagam 10% administration was up to 6 mg/kg/min [0.06 mL/kg/min], which was achieved in 24 of 26 subjects (92%). Subsequently, the maximum infusion rate allowed was 12 mg/kg/min [0.12mL/kg/min], which was achieved in 54 of 90 subjects (60%). Platelet counts were measured on Days 1 to 7, 14, 21, and 63.

The study was designed to determine the response rate defined as the percentage of subjects with an increase in platelet count to at least 50 x 10 ^9 /L within 7 days after the first infusion (responders). Additionally, maximum platelet count, the time to reach a platelet count of at least 50 x 10 ^9 /L within the first 7 days, the duration of that response (i.e. the number of days the platelet count remained in excess of 50 x 10 ^9 /L), and the regression of hemorrhages in subjects who had bleeding at baseline were observed.

Of the 66 subjects with chronic ITP in the efficacy analysis, 54 (82%) responded to Octagam 10% with a rise in platelet counts to at least 50 x 10 ^9 /L within 7 days after the first infusion. The lower bound of the overall 95% confidence interval for the response rate (73%) is above the predefined response rate of 70%.

The mean maximum platelet count achieved in the 66 subjects with chronic ITP was 227 x 10 ^9 /L.

Table 7. Maximum Platelet Count (x10 ^9 /L)

 | Chronic ITP subjects (n=66)
Median and range | 212.0 (18 to 686)
Mean ± s.d. | 227.0 ± 155.63

The median time to reach a platelet response of at least 50 x 10 ^9 /L was 2 days after the first infusion. The duration of platelet response was analyzed for the 54 subjects with chronic ITP who achieved a response within 7 days after the first infusion: the median duration of platelet response in these subjects was 12 days (range: 1 to 79 days).

Table 8. Time to and Duration of Platelet Response (Responders Only).

 | Time to platelet response (days) | Duration of platelet response (days)
 | Chronic ITP subjects (n=54) | Chronic ITP subjects (n=54)
Median and range | 2 (1 to 5) | 12 (1 to 79)
Mean ± s.d. | 1.8 ± 0.91 | 20.9 ± 21.76

In 35 of the 45 subjects with chronic ITP (78%) who had bleeding at baseline, the hemorrhages had completely resolved by Day 7. A decrease in the severity of hemorrhage from baseline to Day 7 was observed in 38 of 45 subjects (84%) with chronic ITP.

Table 9. Assessment of Bleeding at Day 7 in Subjects with Baseline Bleeding

Number of Subjects with Baseline Bleeding |  |  | Severity at Day 7
 | None | Minor | Mild | Moderate | Missing
Chronic ITP (N=45) | 35 (78%) | 8 (18%) | 0 | 0 | 2 (4%)

14.2 Treatment of Dermatomyositis

In a prospective, double-blind, randomized, placebo-controlled, multicenter study, 95 adults with dermatomyositis were enrolled and randomized. Forty-seven subjects received Octagam and 48 subjects received placebo in an initial 16week, double-blind First Period, followed by a 6-month, open-label Extension Period, during which all subjects who were eligible to continue, received Octagam 10% every 4 weeks. Forty-five subjects in the initial Octagam group and 46 subjects in the placebo group entered the Extension Period.

Efficacy in this study was based on the proportion of responders at Week 16. A responder was defined as a subject with a minimal improvement of ≥20 points on the Total Improvement Score (TIS). TIS is based on six Core Set Measures (CSM) which include: Manual Muscle Testing MMT-8, Physician Global Disease Activity (GDA) as part of Myositis Disease Activity Assessment Tool (MDAAT) assessed by the Investigator on a Visual Analog Scale (VAS), Extramuscular Activity as part of MDAAT assessed by the Investigator on a VAS, Patient GDA assessed by the Patient on a VAS, Health Assessment Questionnaire (HAQ) assessed by the Patient, and Muscle Enzymes: aldolase, creatine kinase, alanine aminotransferase (ALT), aspartate aminotransferase (AST), lactate dehydrogenase (LDH).

Table 10 shows the proportion of responders in the Octagam 10% and the placebo groups, and the difference in responder rate between the two groups at Week 16. The median time to response was 35 days in the Octagam 10% group. In addition, there was a greater proportion of subjects in the Octagam 10% group compared to placebo with at least moderate improvement defined as ≥40 points on the TIS and major improvement defined as ≥60 points on the TIS (Table 10).

Table 10. Total Improvement Score – Proportion of Responders by Improvement Category at Week 16

Total Improvement Score (TIS) Response Category | Octagam 10% N=47 Number of Subjects (%) | Placebo N=48 Number of Subjects (%) | Difference in responder proportion Octagam 10% – placebo Point Estimate [95% CI], p-value*
At Least Minimal Improvement (TIS ≥ 20) (Primary Efficacy Endpoint) | 37 (78.7%) | 21 (43.8%) | 35.0% [16.7%, 53.2%], 0.0008
At Least Moderate Improvement (TIS ≥ 40) | 32 (68.1%) | 11 (22.9%) | 45.2% [27.3%, 63.0%]
At Least Major Improvement (TIS ≥ 60) | 15 (32.0%) | 4 (8.3%) | 23.6% [8.1%, 39.0%]

*Cochran-Mantel-Haenszel Test; CI = Confidence interval

Efficacy was further supported by an improvement in the Cutaneous Dermatomyositis Disease Area and Severity Index (CDASI) total activity score, with a mean decrease of 9.4 (SD: 10.5) points from baseline to Week 16 in the Octagam 10% group versus 1.2 (SD: 7.0) point in the placebo group.

The Octagam 10% group maintained their improvement in TIS (32/45, 71.1%) during the 6-month Extension Period. Among the 46 subjects who switched from placebo to Octagam 10% in the Extension Period, 69.6% (32/46) were classified as responders at the end of the 6-month Extension Period.

15 REFERENCES

1. Duhem C, Dicato MA, Ries F: Side-effects of intravenous immune globulins. Clin.Exp.Immunol. 1994;97 Suppl 1:79-83.
2. Kannan S, Rowland CH, Hockings GI, et al: Intragam can interfere with blood glucose monitoring. Med J Aust. 2004;180:251-252.
3. Steinberger BA, Ford SM, Coleman TA: Intravenous immunoglobulin therapy results in post-infusional hyperproteinemia, increased serum viscosity, and pseudohyponatremia. Am.J Hematol. 2003;73:97-100.
4. Dalakas MC: High-dose intravenous immunoglobulin and serum viscosity: risk of precipitating thromboembolic events. Neurology 1994;44:223-226.
5. Go RS, Call TG: Deep venous thrombosis of the arm after intravenous immunoglobulin infusion: case report and literature review of intravenous immunoglobulin-related thrombotic complications. Mayo Clin Proc 2000;75:83-85.
6. Wolberg AS, Kon RH, Monroe DM, et al: Coagulation factor XI is a contaminant in intravenous immunoglobulin preparations. Am.J.Hematol. 2000;65:30-34.
7. Kahwaji J, Barker E, Pepkowitz S, et al: Acute Hemolysis After High-Dose Intravenous Immunoglobulin Therapy in Highly HLA Sensitized Patients. Clinical journal of the American Society of Nephrology : CJASN 2009;DOI:10.2215/CJN.04540709.
8. Daw Z, Padmore R, Neurath D, et al: Hemolytic transfusion reactions after administration of intravenous immune (gamma) globulin: a case series analysis. Transfusion 2008;48:1598-1601.
9. Sekul EA, Cupler EJ, Dalakas MC: Aseptic meningitis associated with high-dose intravenous immunoglobulin therapy: frequency and risk factors. Ann Intern.Med 1994;121:259-262.
10. Rizk A, Gorson KC, Kenney L, et al: Transfusion-related acute lung injury after the infusion of IVIG. Transfusion 2001;41:264-268.
11. Auletta CS, Kotkoskie LA, Saulog T, et al: A dietary oncogenicity study of tributyl phosphate in the CD-1 mouse. Toxicology 1998;128:135-141.
12. Auletta CS, Weiner ML, Richter WR: A dietary toxicity/oncogenicity study of tributyl phosphate in the rat. Toxicology 1998;128:125-134

16 HOW SUPPLIED/STORAGE AND HANDLING

Octagam 10% is supplied in 2 g, 5 g, 10 g, 20 g or 30 g single use bottles.

 | Octagam 10%
Carton NDC Number | Container NDC Number | Size | Grams Protein
0069-6002-02 | 0069-6002-01 | 20 mL | 2.0
0069-6550-02 | 0069-6550-01 | 50 mL | 5.0
0069-6111-02 | 0069-6111-01 | 100 mL | 10.0
0069-6237-02 | 0069-6237-01 | 200 mL | 20.0
0069-6339-02 | 0069-6339-01 | 300 mL | 30.0

Octagam 10% is not supplied with an infusion set. If a filtered infusion set is used (not mandatory), choose a filter size of 0.2 – 200 microns.

Components used in the packaging of Octagam 10% are not made with natural rubber latex.

Store Octagam 10% for 36 months at +2°C to + 8°C (36°F to 46°F) from the date of manufacture. Within this shelf-life, the product may be stored up to 9 months at ≤ +25°C (77°F). After storage at ≤ +25°C (77°F) the product must be used or discarded.

Do not use after expiration date.

Do not freeze. Do not use frozen product.

Dispose of any unused product or waste material in accordance with local requirements.

17 PATIENT COUNSELING INFORMATION

Inform patients of the signs and symptoms of hypersensitivity reactions including urticaria, generalized urticaria, tightness of the chest, wheezing, hypotension, and anaphylaxis, and to contact their physicians immediately if allergic symptoms occur,

Inform patients to immediately report the signs and symptoms of the following conditions to their physician:

• renal failure, such as decreased urine output, sudden weight gain, fluid retention/edema, and/or shortness of breath

• aseptic meningitis, such as headache, neck stiffness, drowsiness, fever, sensitivity to light, painful eye movements, nausea, and vomiting

• hemolysis, such as fatigue, increased heart rate, yellowing of the skin or eyes, and dark-colored urine

• TRALI, such as troubled breathing, chest pain, blue lips or extremities, and fever. TRALI typically occurs within 1 to 6 hours following transfusion

Thrombosis

Instruct patients to immediately report symptoms of thrombosis. These symptoms may include: pain and/or swelling of an arm or leg with warmth over the affected area, discoloration of an arm or leg, unexplained shortness of breath, chest pain or discomfort that worsens on deep breathing, unexplained rapid pulse, numbness or weakness on one side of the body.

Inform patients that Octagam 10% is made from human plasma and may contain infectious agents that can cause disease (e.g., viruses, and, theoretically, the CJD agent), and that the risk of infectious agent transmission has been reduced by (a) screening plasma donors for prior exposure to certain viruses, (b) testing the donated plasma for certain viral infections and (c) inactivating and/or removing certain viruses during manufacture.

Inform patients that administration of Octagam 10% may interfere with the response to live viral vaccines such as measles, mumps and rubella, and to notify their immunizing physician of their therapy with Octagam 10%.

Manufactured by:

Octapharma Pharmazeutika Produktionsges.m.b.H.

Oberlaaer Strasse 235

A-1100 Vienna, Austria

Octapharma AB

Lars Forssells gata 23

SE- 112 75, Sweden

U.S. License No. 1646

PACKAGE LABEL - PRINCIPAL DISPLAY PANEL

Immune Globulin Intravenous (Human), 10%

Octagam 10%

20 mL

NDC 0069-6002-02

Octagam 10%

50 mL

NDC 0069-6550-02

Octagam 10%

100 mL

NDC 0069-6111-02

Octagam 10%

200 mL

NDC 0069-6237-02

Octagam 10%

300 mL

NDC 0069-6339-02